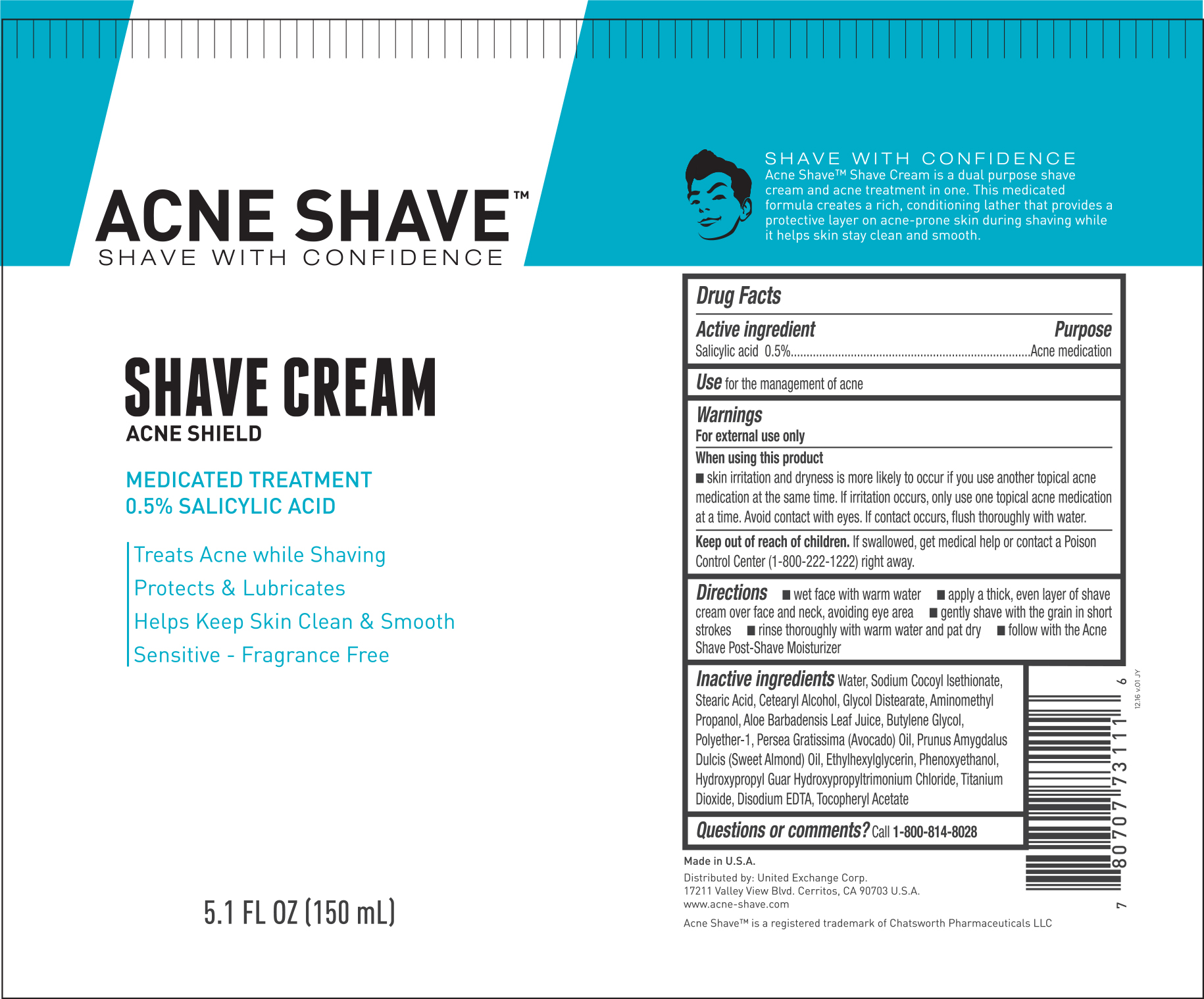 DRUG LABEL: Acne Shave Cream
NDC: 65923-111 | Form: CREAM
Manufacturer: United Exchange Corp.
Category: otc | Type: HUMAN OTC DRUG LABEL
Date: 20170725

ACTIVE INGREDIENTS: SALICYLIC ACID 0.5 mg/1 mL
INACTIVE INGREDIENTS: WATER; SODIUM COCOYL ISETHIONATE; STEARIC ACID; CETOSTEARYL ALCOHOL; GLYCOL DISTEARATE; AMINOMETHYLPROPANOL; ALOE VERA LEAF; BUTYLENE GLYCOL; AVOCADO OIL; ALMOND OIL; ETHYLHEXYLGLYCERIN; PHENOXYETHANOL; TITANIUM DIOXIDE; EDETATE DISODIUM; .ALPHA.-TOCOPHEROL ACETATE

Active ingredient Purpose

Salicylic acid 0.5%................................................Acne medication

Uses

for the management of acne

Warnings

For external use only

When using this product

- skin irriation and dryness is more likely to occur if you use another topical acne medication at the same time. If irritation occurs, only use one

topical acne medication at a time. Avoid contact with the eyes. If contact occurs, flush thoroughly with water.

Keep out of reach of children.

If swallowed, get medical help or contact a Poison Control Center (1-800-222-1222) right away.

Directions

- wet face with warm water
- apply a thick, even layer of shave cream over face and neck, avoid eye area
- gently shave with the grain in short strokes
- rinses throughly with warm water and pat dry
- follow with the Acne Shave Post-Shave Moisturizer

Inactive ingredients

Water, Sodium Cocoyl Isethionate, Stearic Acid, Cetearyl Alcohol, Glycol Distearate, Aminomethyl Propanol, Aloe Barbadensis Leaf Juice,

Butylene Glycol, Polyether-1, Persea Gratissima (Avocado) Oil, Prunus Amygdalus Dulcis (Sweet Almond) Oil, Ethylhexylglycerin,

Phenoxyethanol, Hydroxypropyl Guar Hydroxypropyltrimonium Chloride, Titanium Dioxide, Disodium EDTA, Tocopheryl Acetate

DOSAGE AND ADMINISTRATION

Distributed by:

United Exchange Corp.

17211 Valley View Ave.

Cerritos, CA 90703

Made in U.S.A.

www.acne-shave.com